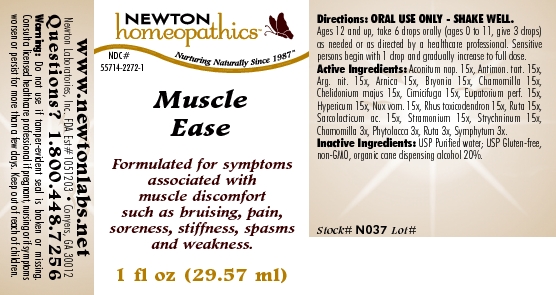 DRUG LABEL: Muscle Ease 
NDC: 55714-2272 | Form: LIQUID
Manufacturer: Newton Laboratories, Inc.
Category: homeopathic | Type: HUMAN OTC DRUG LABEL
Date: 20110301

ACTIVE INGREDIENTS: Aconitum Napellus 15 [hp_X]/1 mL; Antimony Potassium Tartrate 15 [hp_X]/1 mL; Silver Nitrate 15 [hp_X]/1 mL; Arnica Montana 15 [hp_X]/1 mL; Bryonia Alba Root 15 [hp_X]/1 mL; Matricaria Recutita 15 [hp_X]/1 mL; Chelidonium Majus 15 [hp_X]/1 mL; Black Cohosh 15 [hp_X]/1 mL; Eupatorium Perfoliatum Flowering Top 15 [hp_X]/1 mL; Hypericum Perforatum 15 [hp_X]/1 mL; Strychnos Nux-vomica Seed 15 [hp_X]/1 mL; Toxicodendron Pubescens Leaf 15 [hp_X]/1 mL; Ruta Graveolens Flowering Top 15 [hp_X]/1 mL; Lactic Acid, L- 15 [hp_X]/1 mL; Datura Stramonium 15 [hp_X]/1 mL; Strychnine 15 [hp_X]/1 mL; Matricaria Recutita 3 [hp_X]/1 mL; Phytolacca Americana Root 3 [hp_X]/1 mL; Ruta Graveolens Flowering Top 3 [hp_X]/1 mL; Comfrey Root 3 [hp_X]/1 mL
INACTIVE INGREDIENTS: Alcohol

Muscle Ease

INDICATIONS & USAGE SECTION

Muscle Ease Formulated for symptoms associated with muscle discomfort such as bruising, pain, soreness, stiffness, spasms and weakness.

DOSAGE & ADMINISTRATION SECTION

Directions: ORAL USE ONLY - SHAKE WELL. Ages 12 and up, take 6 drops orally (ages 0 to 11, give 3 drops) as needed or as directed by a healthcare professional. Sensitive persons begin with 1 drop and gradually increase to full dose.

OTC - ACTIVE INGREDIENT SECTION

Aconitum nap. 15x, Antimon. tart. 15x, Arg. nit. 15x, Arnica 15x, Bryonia 15x, Chamomilla 15x, Chelidonium majus 15x, Cimicifuga 15x, Eupatorium perf. 15x, Hypericum 15x, Nux vom. 15x, Rhus toxicodendron 15x, Ruta 15x,Sarcolacticum ac. 15x, Stramonium 15x, Strychninum 15x, Chamomilla 3x, Phytolacca 3x, Ruta 3x, Symphytum 3x.

OTC - PURPOSE SECTION

Formulated for symptoms associated with muscle discomfort such as bruising, pain, soreness, stiffness, spasms and weakness.

INACTIVE INGREDIENT SECTION

Inactive Ingredients: USP Purified Water; USP Gluten-free, non-GMO, organic cane dispensing alcohol 20%.

QUESTIONS SECTION

www.newtonlabs.net Newton Laboratories, Inc. FDA Est # 1051203 - Conyers, GA 30012
Questions? 1.800.448.7256

WARNINGS SECTION

Warning: Do not use if tamper - evident seal is broken or missing. Consult a licensed healthcare professional if pregnant, nursing or if symptoms worsen or persist for more than a few days. Keep out of reach of children

OTC - PREGNANCY OR BREAST FEEDING SECTION

Consult a licensed healthcare professional if pregnant, nursing or if symptoms worsen or persist for more than a few days.

OTC - KEEP OUT OF REACH OF CHILDREN SECTION

Keep out of reach of children